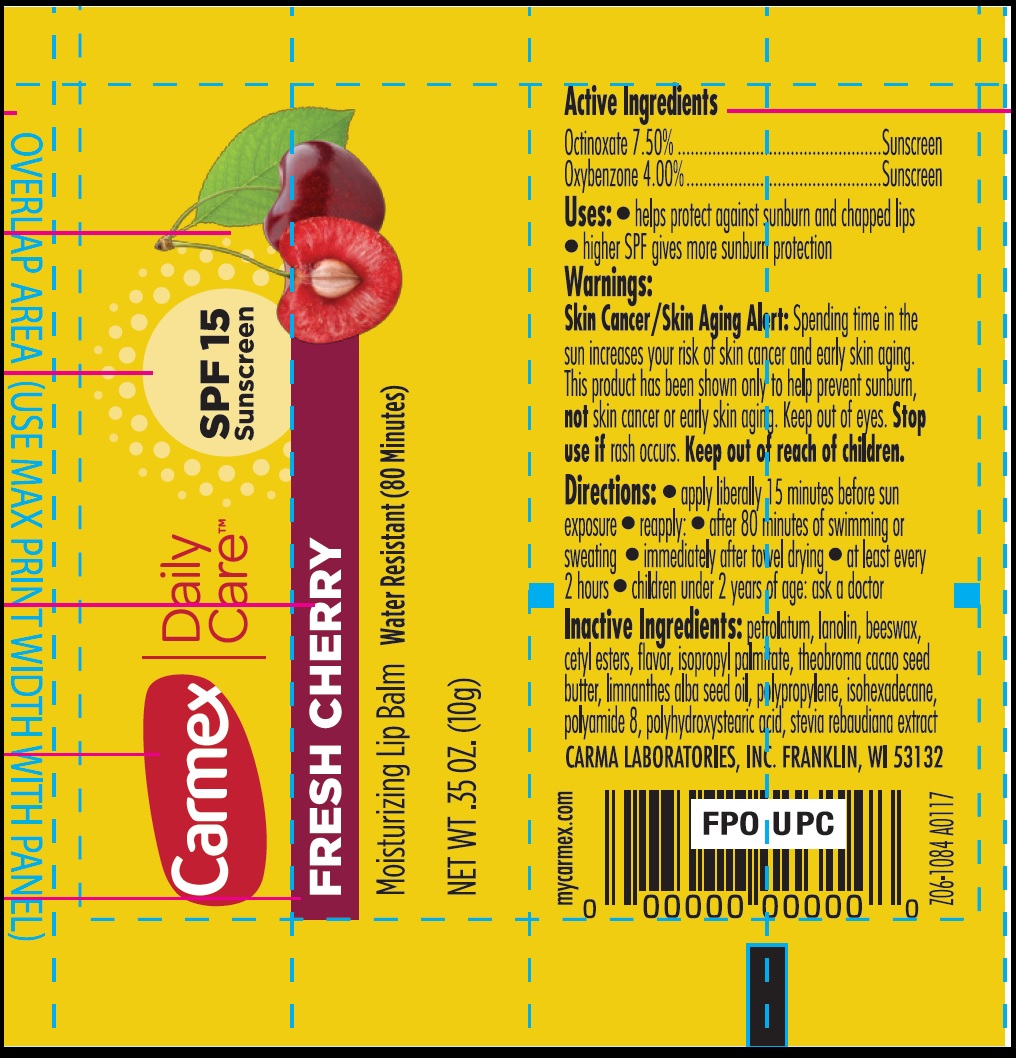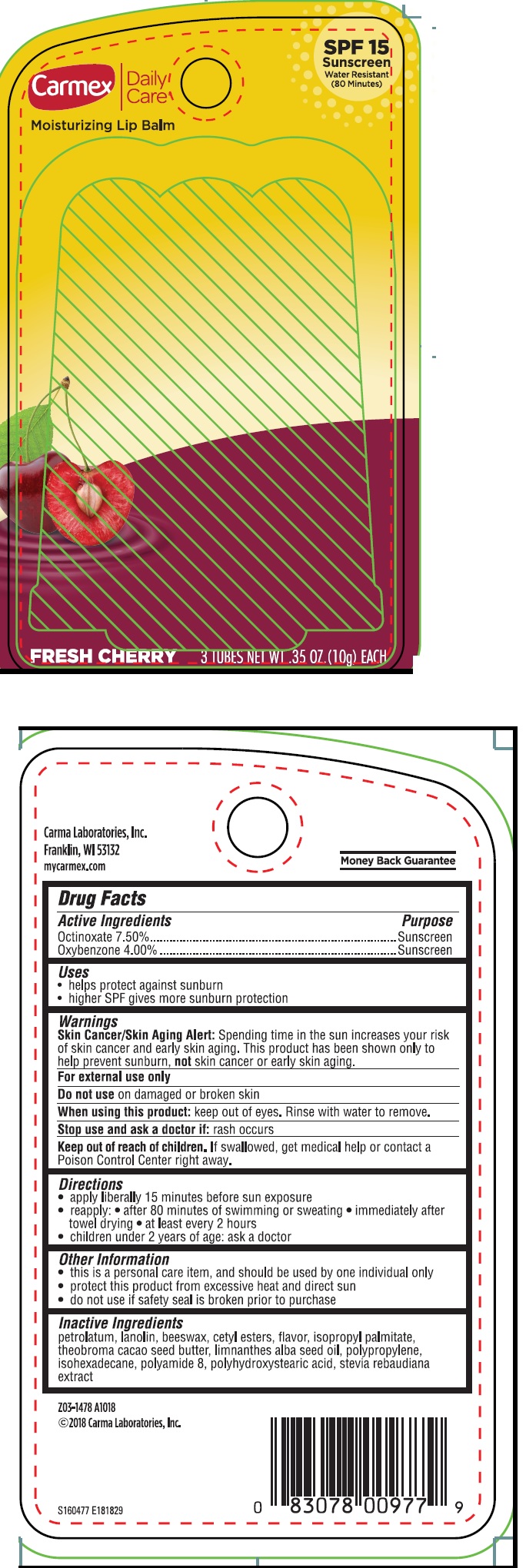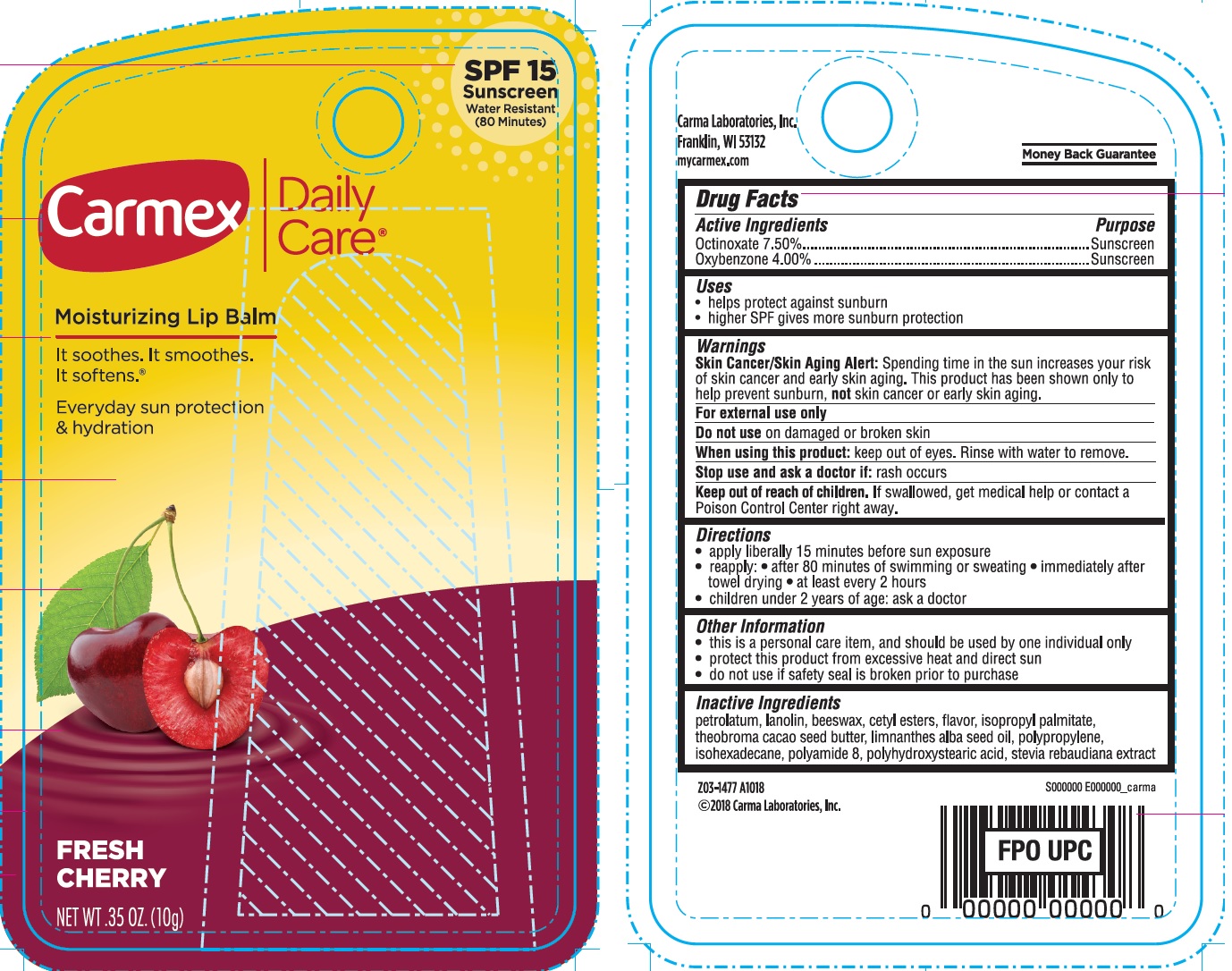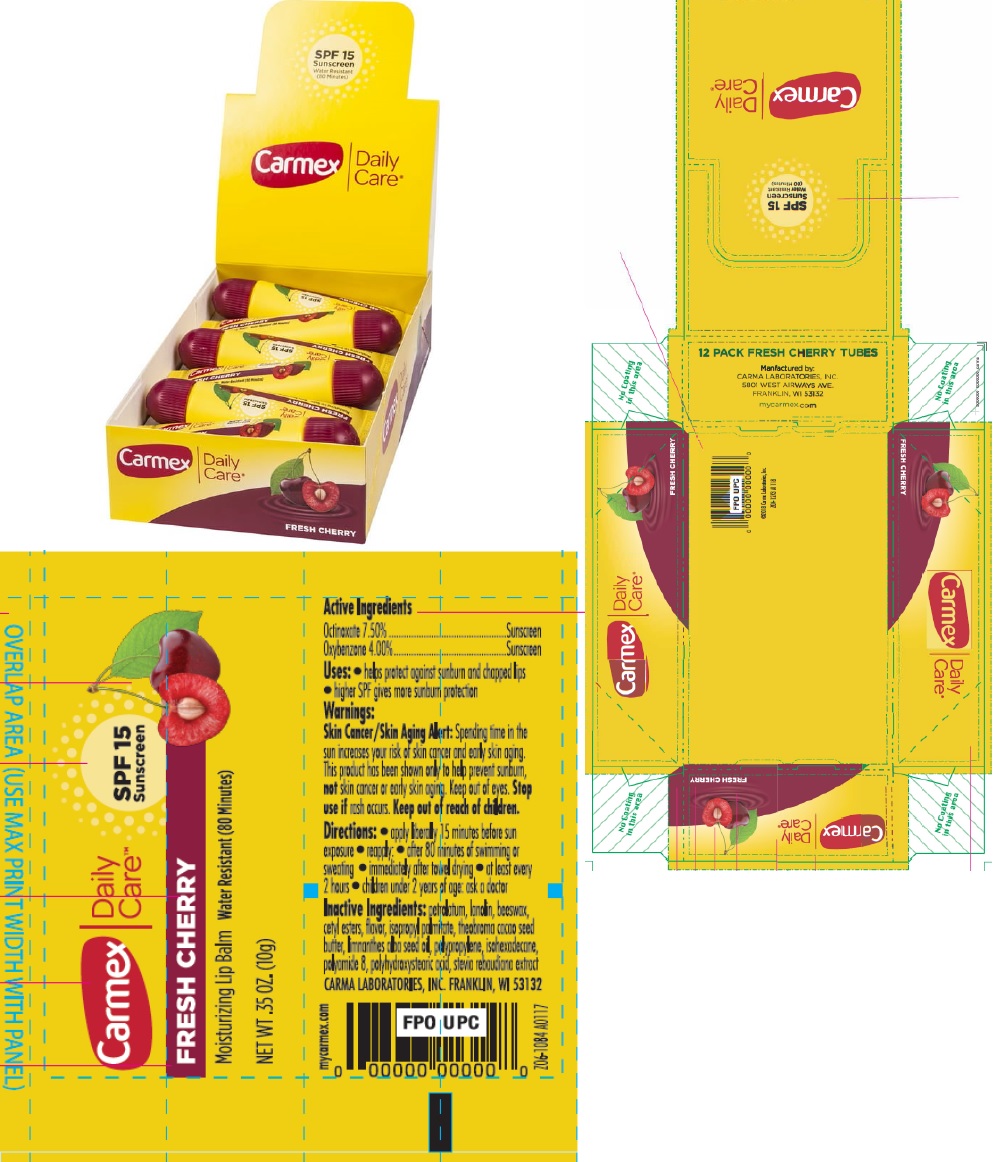 DRUG LABEL: Carmex Daily Care Moisturizing Lip Balm Fresh Cherry SPF 15
NDC: 10210-0029 | Form: SALVE
Manufacturer: Carma Laboratories, Inc.
Category: otc | Type: HUMAN OTC DRUG LABEL
Date: 20231025

ACTIVE INGREDIENTS: OCTINOXATE 75 mg/1 g; OXYBENZONE 40 mg/1 g
INACTIVE INGREDIENTS: YELLOW WAX; PETROLATUM; LANOLIN; CETYL ESTERS WAX; ISOPROPYL PALMITATE; MEADOWFOAM SEED OIL; ISOHEXADECANE

Carmex Daily Care Moisturizing Lip Balm Fresh Cherry SPF 15

Active Ingredients

Octinoxate 7.50%

Oxybenzone 4.00%

Purpose

Sunscreen

Uses

- helps protect against sunburn and chapped lips
- higher SPF gives more sunburn protection

Warnings

Spending time in the sun increases your risk of skin cancer and early skin aging. This product has been shown only to help prevent sunburn, skin cancer or early skin aging. Skin Cancer/Skin Aging Alert: not

For external use only

Do not use

on damaged or broken skin

When using this poduct:

keep out of eyes. Rinse with water to remove.

Stop use and ask a doctor if:

rash occurs.

Keep out of reach of children.

If swallowed, get medical help or contact a Poison Control Center right away.

Directions:

- apply liberally 15 minutes before sun exposure • reapply: • after 80 minutes of swimming or sweating • immediately after towel drying • at least every 2 hours • children under 2 years: Ask a doctor

Other Information

- this is a personal care item, and should be used by one individually only
- protect this product from excessive heat and direct sun
- do not use if safety seal is broken prior to purchase

Inactive Ingredients:

petrolatum, lanolin, beeswax, cetyl esters, flavor, isopropyl palmitate, theobroma cacao seed butter, limnanthes alba seed oil, polypropylene, isohexadecane, polyamide 8, polyhydroxystearic acid, stevia rebaudiana extract